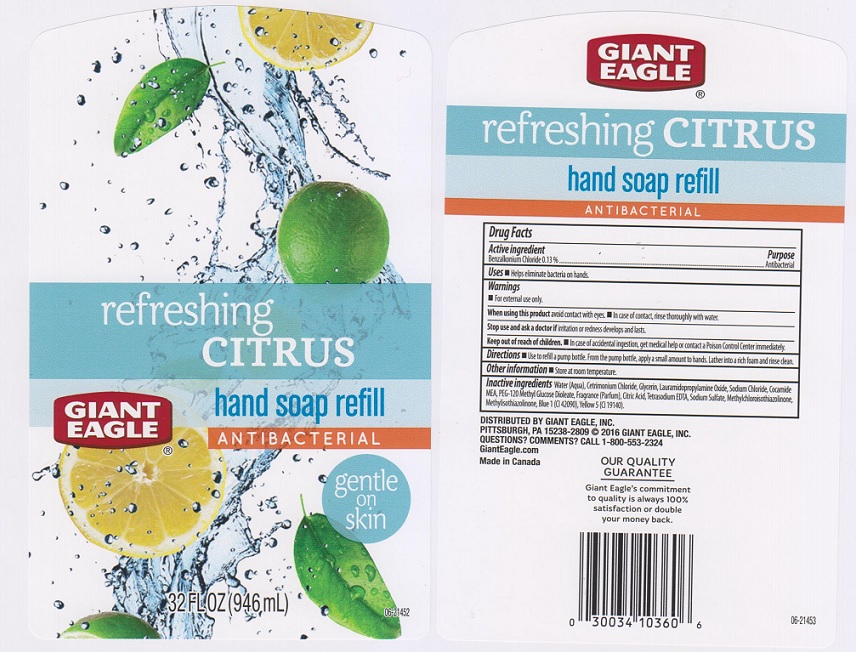 DRUG LABEL: Giant Eagle Refreshing Citrus
NDC: 63148-724 | Form: LIQUID
Manufacturer: Apollo Health and Beauty Care
Category: otc | Type: HUMAN OTC DRUG LABEL
Date: 20161031

ACTIVE INGREDIENTS: BENZALKONIUM CHLORIDE 1.3 mg/1 mL
INACTIVE INGREDIENTS: WATER; CETRIMONIUM CHLORIDE; GLYCERIN; LAURAMIDOPROPYLAMINE OXIDE; SODIUM CHLORIDE; COCO MONOETHANOLAMIDE; PEG-120 METHYL GLUCOSE DIOLEATE; CITRIC ACID MONOHYDRATE; EDETATE SODIUM; SODIUM SULFATE; METHYLCHLOROISOTHIAZOLINONE; METHYLISOTHIAZOLINONE; FD&C BLUE NO. 1; FD&C YELLOW NO. 5

Drug Facts

Active ingredient

Benzalkonium chloride 0.13%

Purpose

Antibacterial

Uses

Helps eliminate bacteria on hands

Warnings

For external use only

When using the product

Avoid contact with eyes. In case of contact, rinse thoroughly with water.

Stop use and ask a doctor if

irritation or redness develops and lasts.

Keep out of reach of children.

In case of accidental ingestion, get medical hlep or contact a Poison Control Center immediately.

Directions

Use to refill a pump bottle. From the pump bottle, apply a small amount to hands. Lather into a rich foam and rinse clean.

Other information

Store at room temperature

Inactive ingredients

Water (Aqua), Cetrimonium Chloride, Glycerin, Lauramidopropylamine Oxide, Sodium Chloride, Cocamide MEA, PEG-120 Methyl Glucose Dioleate, Fragrance (Parfum0, Citric Acid, Tetrasodium EDTA, Sodium Sulfate, Methylchloroisothiazolinone, Methylisothiazolinone, Blue 1 (CI 42090), Yellow 5 (CI 19140).